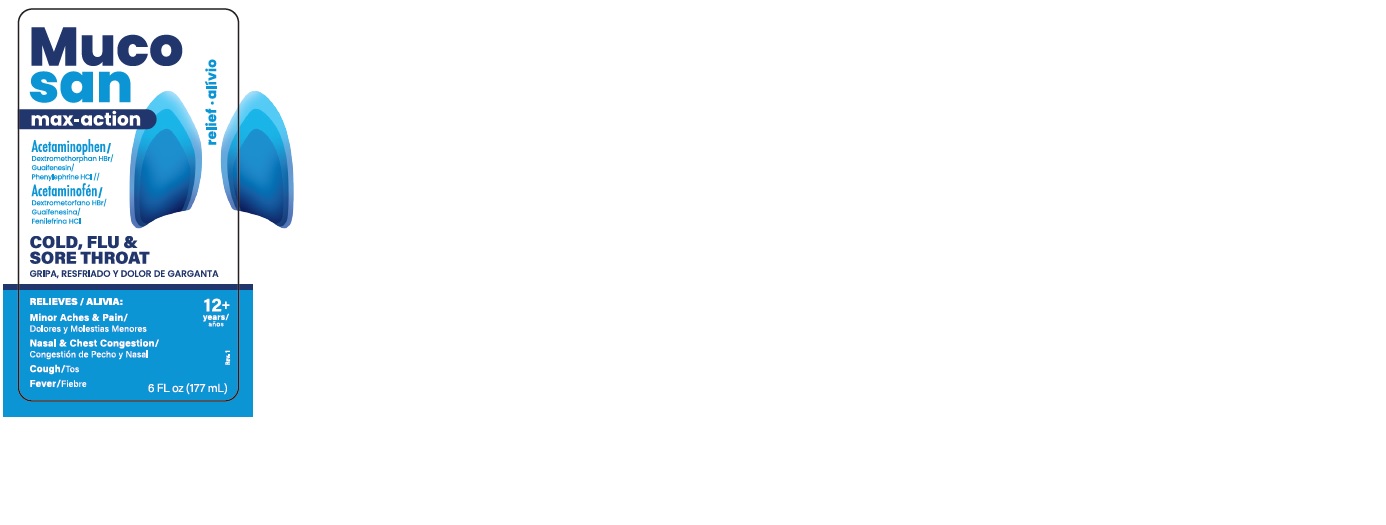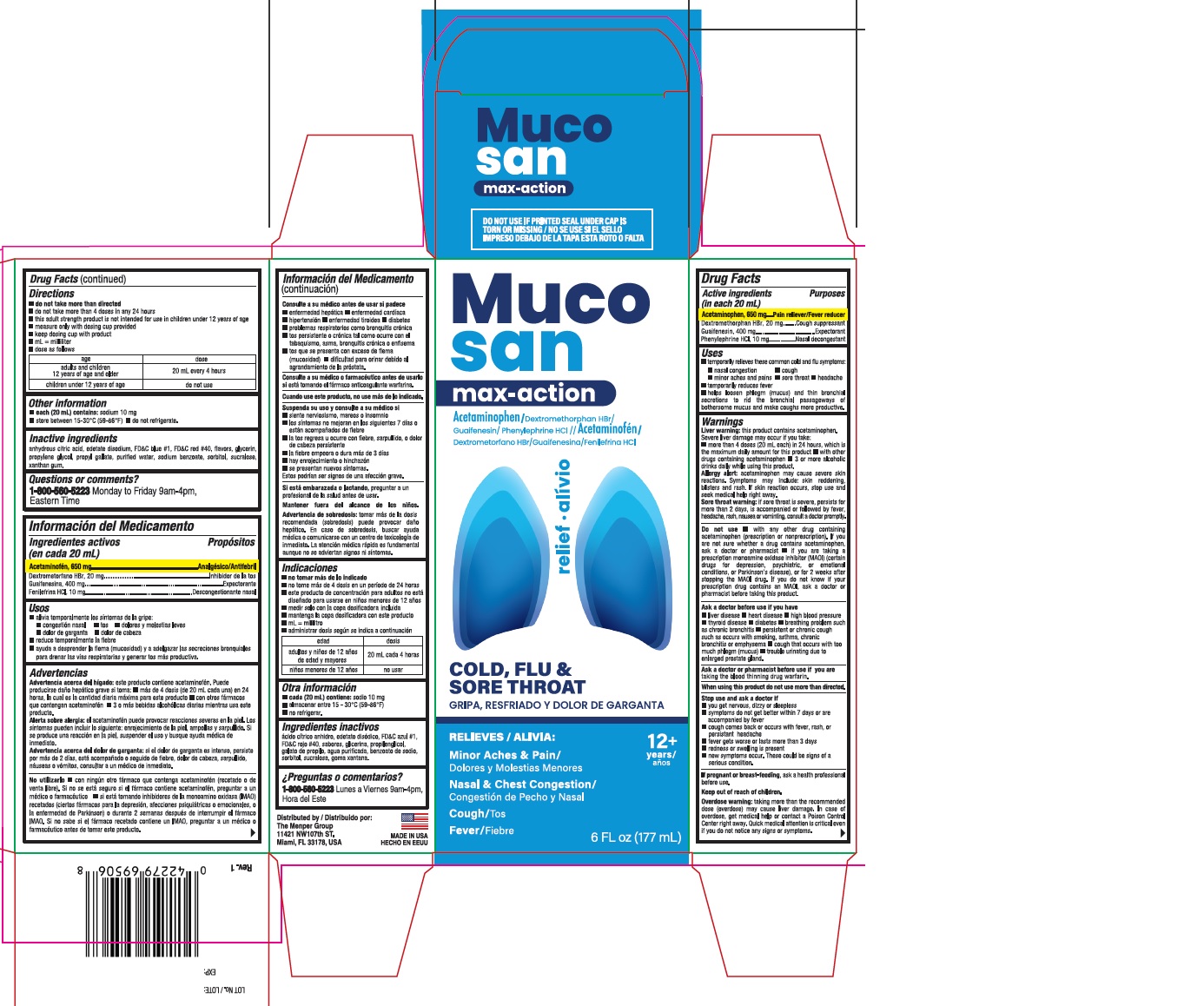 DRUG LABEL: Mucosan Max with Acetaminophen
NDC: 53145-696 | Form: LIQUID
Manufacturer: Menper Distributors, Inc.
Category: otc | Type: HUMAN OTC DRUG LABEL
Date: 20260108

ACTIVE INGREDIENTS: ACETAMINOPHEN 650 mg/20 mL; GUAIFENESIN 400 mg/20 mL; DEXTROMETHORPHAN HYDROBROMIDE 20 mg/20 mL; PHENYLEPHRINE HYDROCHLORIDE 10 mg/20 mL
INACTIVE INGREDIENTS: GLYCERIN; SUCRALOSE; PROPYLENE GLYCOL; PROPYL GALLATE; ANHYDROUS CITRIC ACID; FD&C RED NO. 40; EDETATE DISODIUM; XANTHAN GUM; WATER; SODIUM BENZOATE; SORBITOL; FD&C BLUE NO. 1

Mucosan Max with Acetaminophen

Active Ingredients (in each 20 mL) Purpose

Acetaminophen, 650 mg................................Pain reliever/Fever reducer

Dextromethorphan HBr, 20 mg......................Cough suppressant

Guaifenesin, 400 mg.............................. .......Expectorant

Phenylephrine HCl, 10 mg.............................Nasal Decongestant

PURPOSE

Pain reliever/Fever reducer

Cough suppressant

Expectorant

Nasal Decongestant

Uses

- temporarily relieves these common cold and flu symptoms:
- nasal congestion
- cough
- minor aches and pains
- sore throat
- headache
- temporarily reduces fever
- helps loosen phlem (mucus) and thin bronchial secretions to rid the bronchial passageways of bothersome mucus and make coughs more productive.

Warnings

Liver warning:this product contains acetaminophen.

Severe liver damage may occur if you take:

- more than 4 doses (20 mL each) in 24 hours, wich is the maximum daily amount for this product
- with other drugs containing acetaminophen
- 3 or more alcoholic drinks daily while using this product.

Allergy alert:acetaminophen may cause severe skin reactions. Symptoms may include: skin reddening, blisters and rash. If skin reaction occurs, stop use and seek medical help right away.

Sore throat warning:if sore throat is severe, persists for more than 2 days, is accompanied or followed by fever, headache, rash, nausea or vomiting, consult a doctor promptly.

Do not use

- With any other drug containing acetamonophen (prescription or nonprescription). If you are not sure whether a drug contains acetaminophen, ask a doctor or pharmacist
- if you are taking a prescription monoamine oxidase inhibitor (MAOI) (certain drugs for depression, psychiatric, or emotional conditions, or Parkinson's disease), or for 2 weeks after stopping the MAOI drug. If you do not know if your prescription drug contains a MAOI, ask a doctor or Pharmacist before taking this product.

Ask a doctor before use if you have

- liver disease
- heart disease
- high blood pressure
- thyroid disease
- diabetes
- breathing problem such as chronic bronchitis
- persistent or chronic cough such as occurs with smoking, asthma, chronic bronchitis or emphysema
- cough that occurs with too much phlegm (mucus)
- trouble urination due to enlarged prostate gland.

Ask a doctor or pharmacist before use if you aretaking the blood thinning drug warfarin.

When using this product do not use more than direct.

Stop use and ask a doctor if

- you get nervous, dizzy or sleepless
- symptoms do not get better within 7 days or are accompanied by fever
- cough comes back or occurs with fever, rash, or persistant headache
- fever gets worse or lasts more than 3 days
- redness or swelling is present
- new symptoms occur. These could be signs of a serious condition.

PREGNANCY OR BREAST FEEDING

If pregnant or breast - feeding, ask a health professional before use.

Keep out of reach of children.

OVERDOSAGE

Overdose warning:taking more than the recommended dose (overdose) may cause liver damage. In case of overdose, get medical help or contact a Poison Control Center right away. Quick medical attention is critical even if you do not notice any signs or symptoms.

Directions

- do not take more than direct
- do not take more than 4 doses in any 24 hours
- this adult strength product is not intended for use in children under 12 years of age
- measure only with dosing cup provided
- keep dosing cup with product
- mL = milliliter
- dose as follows

age | dose
adults and children 12 years of age and older | 20 mL every 4 hours
children under 12 years of age | do not use

Other information

- each (20 mL) contains:sodium 10mg
- store between 15-30°C (59-86°F)
- do not refrigerate.

INACTIVE INGREDIENT

anhydrous citric acid, edetate disodium, FD&C blue #1, FD&C red #40, flavors, glycerin, propylene glycol, propyl gallate, purified water, sodium benzoate, sorbitol, sucralose, xanthan gum.

Questions or comments?

1-800-560-5223Monday to Friday 9am-4pm, Eastern Time